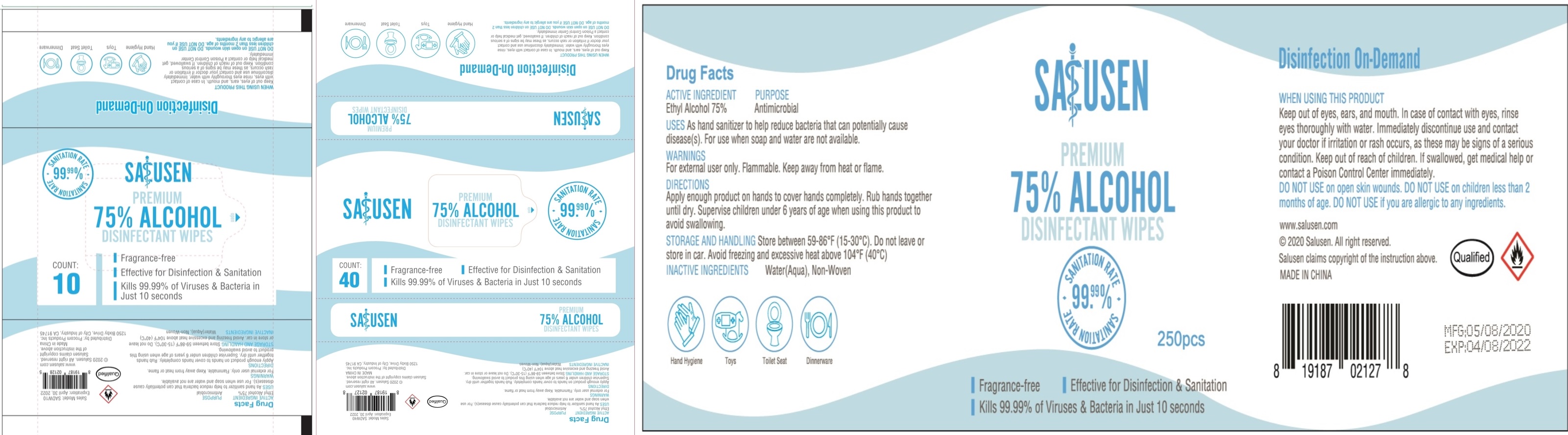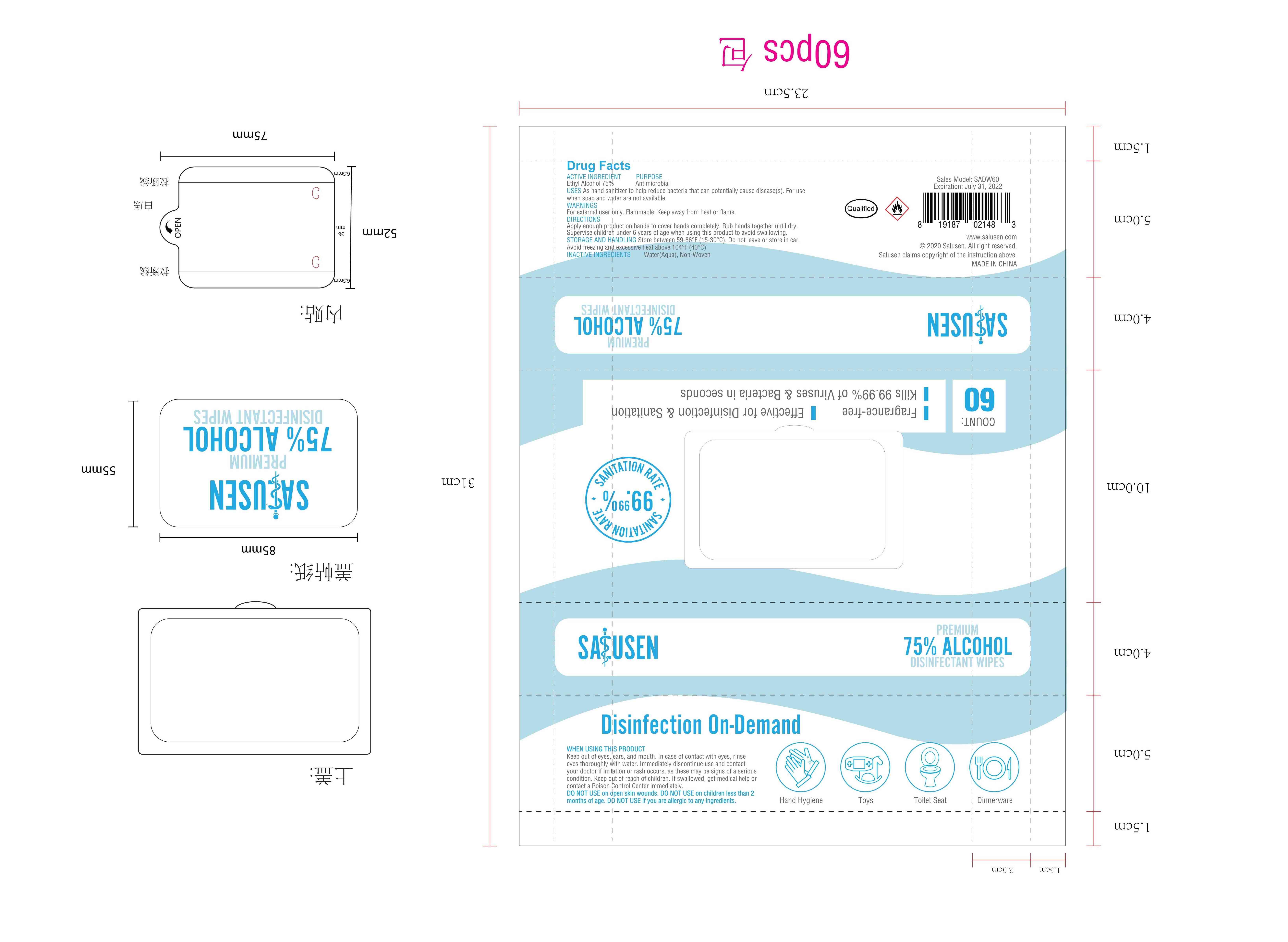 DRUG LABEL: Salusen 75%Alcohol Wipes
NDC: 43116-006 | Form: CLOTH
Manufacturer: Shenzhen Shierjie Biological Engineering Co., LTD
Category: otc | Type: HUMAN OTC DRUG LABEL
Date: 20201122

ACTIVE INGREDIENTS: ALCOHOL 75 mL/100 1
INACTIVE INGREDIENTS: WATER

43116-006
Salusen 75%Alcohol Wipes

Active Ingredient

Ethyl Alcohol 75%

Purpose

Antimicrobial

Uses

As hand sanitizer to help reduce bacteria that can potentially cause disease(s) For use when soap and water are not available

Warnings

For external user only Flammable Keep away from heat or flame

DO NOT USE on open skin wounds. DO NOT USE on children less than 2 months of age. DO NOT USE if you are allergic to any ingredients

WHEN USING

Keep out of eyes,ears, and mouth. In case of contact with eyes, rinse eyes thoroughly With water. Immediately discontinue use and contact your doctor if irritation or rash occurs, as these may be signs of a serious condition. Keep out of reach of children. If swallowed, get medical help or contact a Poison Control Center immediately

STOP USE

/

Keep out of reach of children. If swallowed, get medical help or contact a Poison Control Center immediately

Directions

Apply enough product on hands to cover hands completely. Rub hands together until dry.
Supervise childreh under 6 years of age when using this product to avoid swallowing.

Other information

Store between 59-86F(15-30.C). Do not leave or store in car. Avoid freezing and excessive heat above 104°F(40°C)

Inactive ingredients

Water(Aqua),Non-woven